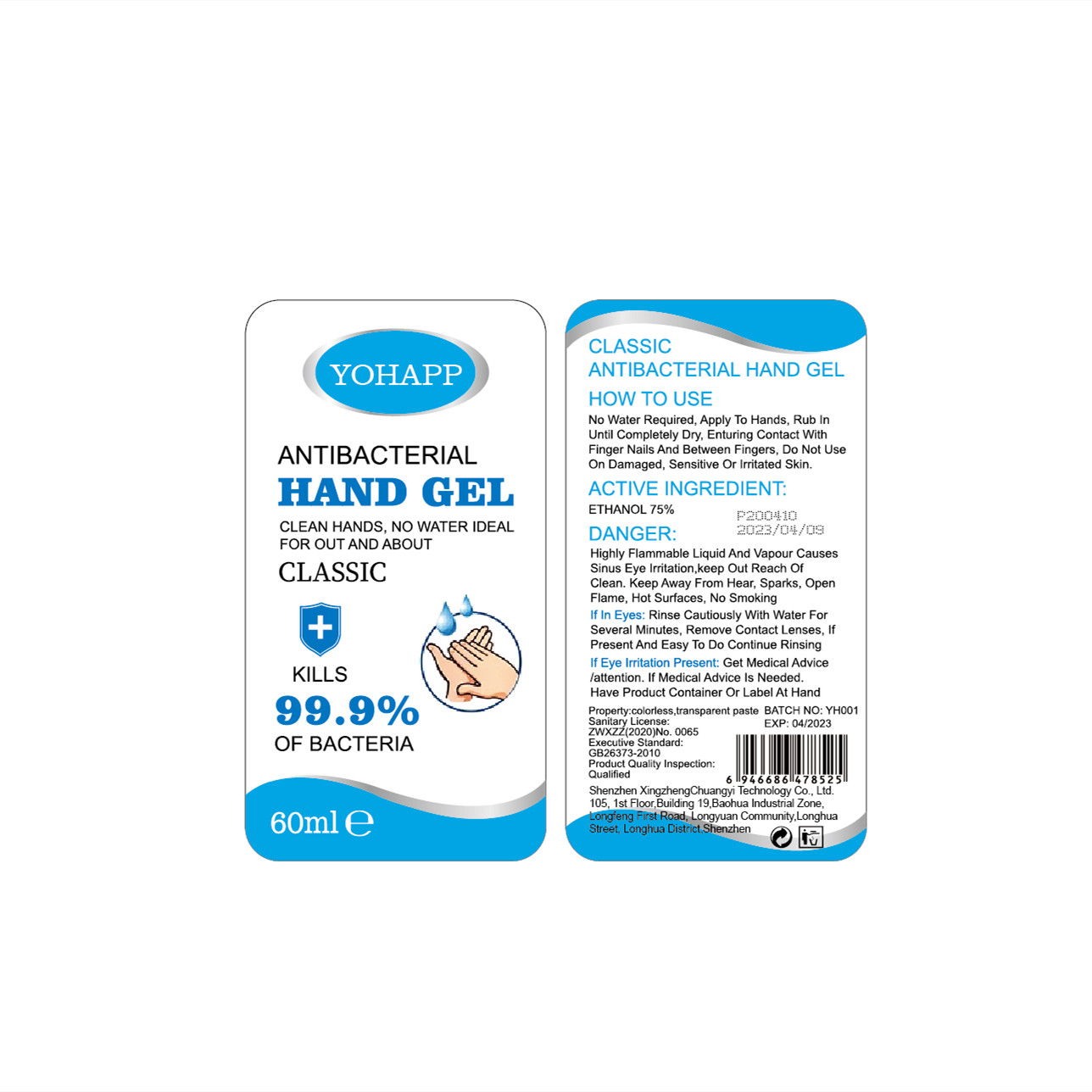 DRUG LABEL: Disinfecting Hand Sanitizer
NDC: 40336-001 | Form: GEL
Manufacturer: Shenzhen Xingzheng Chuangyi Technology Co., Ltd.
Category: otc | Type: HUMAN OTC DRUG LABEL
Date: 20200424

ACTIVE INGREDIENTS: ALCOHOL 45 mL/60 mL
INACTIVE INGREDIENTS: WATER

DOSAGE AND ADMINISTRATION

Keep Away From Hear, Sparks, Open Flame.

INACTIVE INGREDIENT

water

INDICATIONS AND USAGE

Rinse Cautiously With Water For Several Minutes, Remove Contact Lenses, If Present And Easy To Do Continue Rinsing

ACTIVE INGREDIENT

ETHANOL

keep out of children

PURPOSE

Disinfection
Sterilization
No Rinseing

WARNINGS

If Medical Advice Is Needed.Have Product Container Or Label At Hand